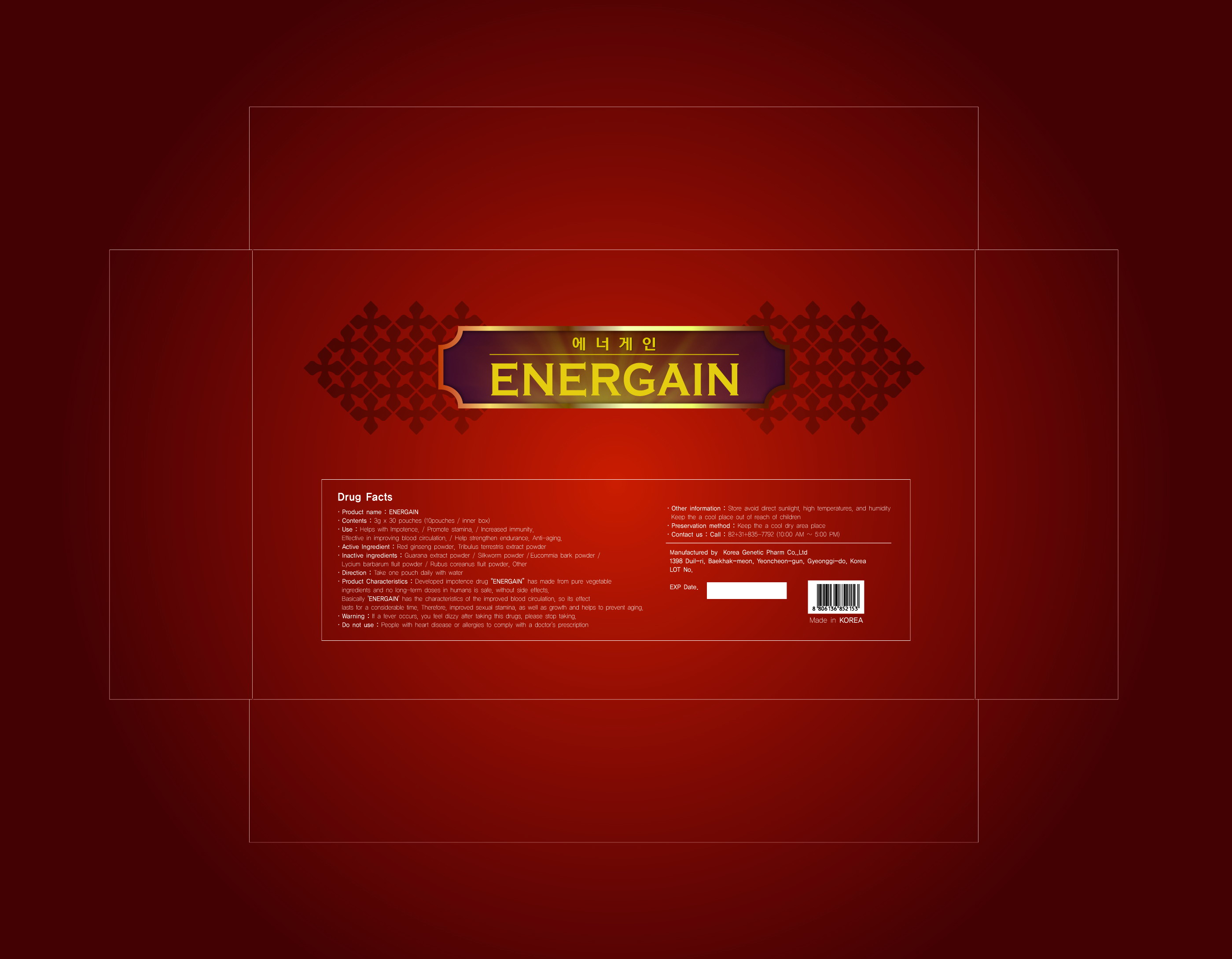 DRUG LABEL: Energain
NDC: 42707-2001 | Form: GRANULE
Manufacturer: Korea Genetic Pharm Co., Ltd 
Category: otc | Type: HUMAN OTC DRUG LABEL
Date: 20120215

ACTIVE INGREDIENTS: TRIBULUS TERRESTRIS ROOT 8 g/100 g
INACTIVE INGREDIENTS: PAULLINIA CUPANA SEED; PANAX GINSENG FRUIT; EUCOMMIA ULMOIDES BARK; LYCIUM BARBARUM FRUIT

Drug Facts

active ingredient: tribulus terrestris extract powder

INACTIVE INGREDIENT

guarana extract powder, silkworm powder, eucommia bark powder, lycium barbarum fruit powder, rubus coreanus fruit powder, red ginseng powder

PURPOSE

helps with impotence, promote stamina, increase immunity, effective in improving blood circulation, helps strengthen endurance, anti-aging

keep out of reach of the children

INDICATIONS AND USAGE

take one pouch daily with water

WARNINGS

if a fever occurs or you feel dizzy after taking this drugs, immediately stop taking

DOSAGE AND ADMINISTRATION

people with heart disease or allergies to comply with a doctor's prescription